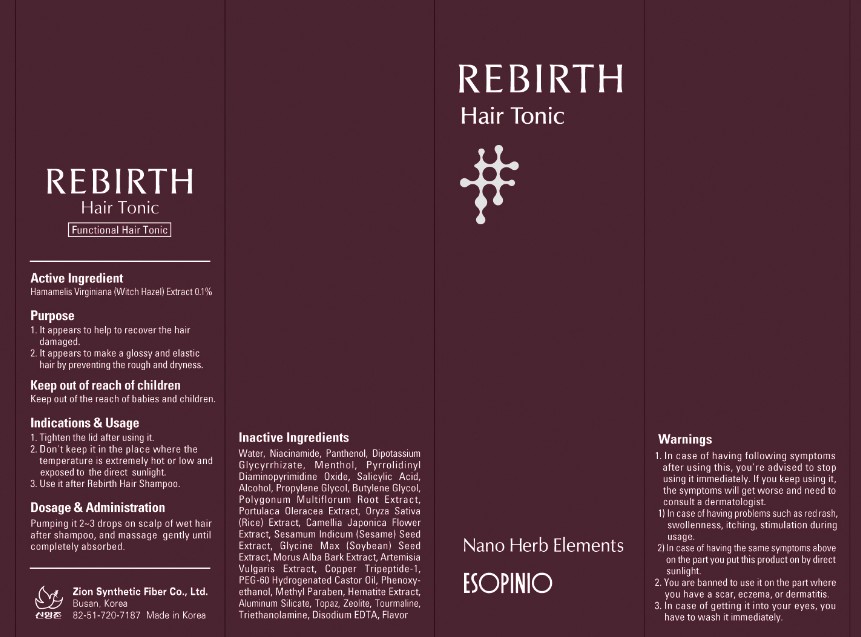 DRUG LABEL: REBIRTH HAIR TONIC
NDC: 44781-190 | Form: SOLUTION
Manufacturer: ZION SYNTHETIC FIBER CO., LTD.
Category: otc | Type: HUMAN OTC DRUG LABEL
Date: 20110918

ACTIVE INGREDIENTS: WITCH HAZEL 0.13 mL/130 mL
INACTIVE INGREDIENTS: Water; NIACINAMIDE; PANTHENOL; Menthol; SALICYLIC ACID; ALCOHOL; Propylene Glycol; BUTYLENE GLYCOL; FALLOPIA MULTIFLORA ROOT; PURSLANE; CAMELLIA JAPONICA FLOWER; SESAME OIL; SOYBEAN; MORUS ALBA POLLEN; ARTEMISIA VULGARIS POLLEN; POLYOXYL 60 HYDROGENATED CASTOR OIL; Phenoxyethanol; METHYLPARABEN; TROLAMINE; EDETATE DISODIUM

Drug Facts

Active ingredient: WITCH HAZEL 0.1%

Inactive ingredients:
Water, Niacinamide, Panthenol, Dipotassium Glycyrrhizate, Menthol, Pyrrolidinyl Diaminopyrimidine Oxide, Salicylic Acid, Alcohol, Propylene Glycol, Butylene Glycol, Polygonum Multiflorum Root Extract, Portulaca Oleracea Extract, Oryza Sativa (Rice) Extract, Camellia Japonica Flower Extract, Sesamum Indicum (Sesame) Seed Extract, Glycine Max (Soybean) Seed Extract, Morus Alba Bark Extract, Artemisia Vulgaris Extract, Copper Tripeptide-1, PEG-60 Hydrogenated Castor Oil, Phenoxyethanol, Methyl Paraben, Hematite Extract, Aluminum Silicate, Topaz, Zeolite, Tourmaline, Triethanolamine, Disodium EDTA, Flavor

Purpose:
It appears to help to recover the hair damaged.
It appears to make a glossy and elastic hair by preventing the rough and dryness.

Warnings:
In case of having following symptoms after using this, you're advised to stop using it immediately. If you keep using it, the symptoms will get worse and need to consult a dermatologist.
- In case of having problems such as red rash, swollenness, itching, stimulation during usage.
- In case of having the same symptoms above on the part you put this product on by direct sunlight.
You are banned to use it on the part where you have a scar, eczema, or dermatitis.
In case of getting it into your eyes, you have to wash it immediately.

Keep out of reach of children:
Keep out of the reach of babies and children.

Indication and usage:
Tighten the lid after using it.
Don't keep it in the place where the temperature is extremely hot or low and exposed the direct sunlight.
Use it after Rebirth Hair Shampoo.

Dosage and administration:
Pumping it 2-3 drops on scalp of wet hair after shampoo, and massage gently until completely absorbed.